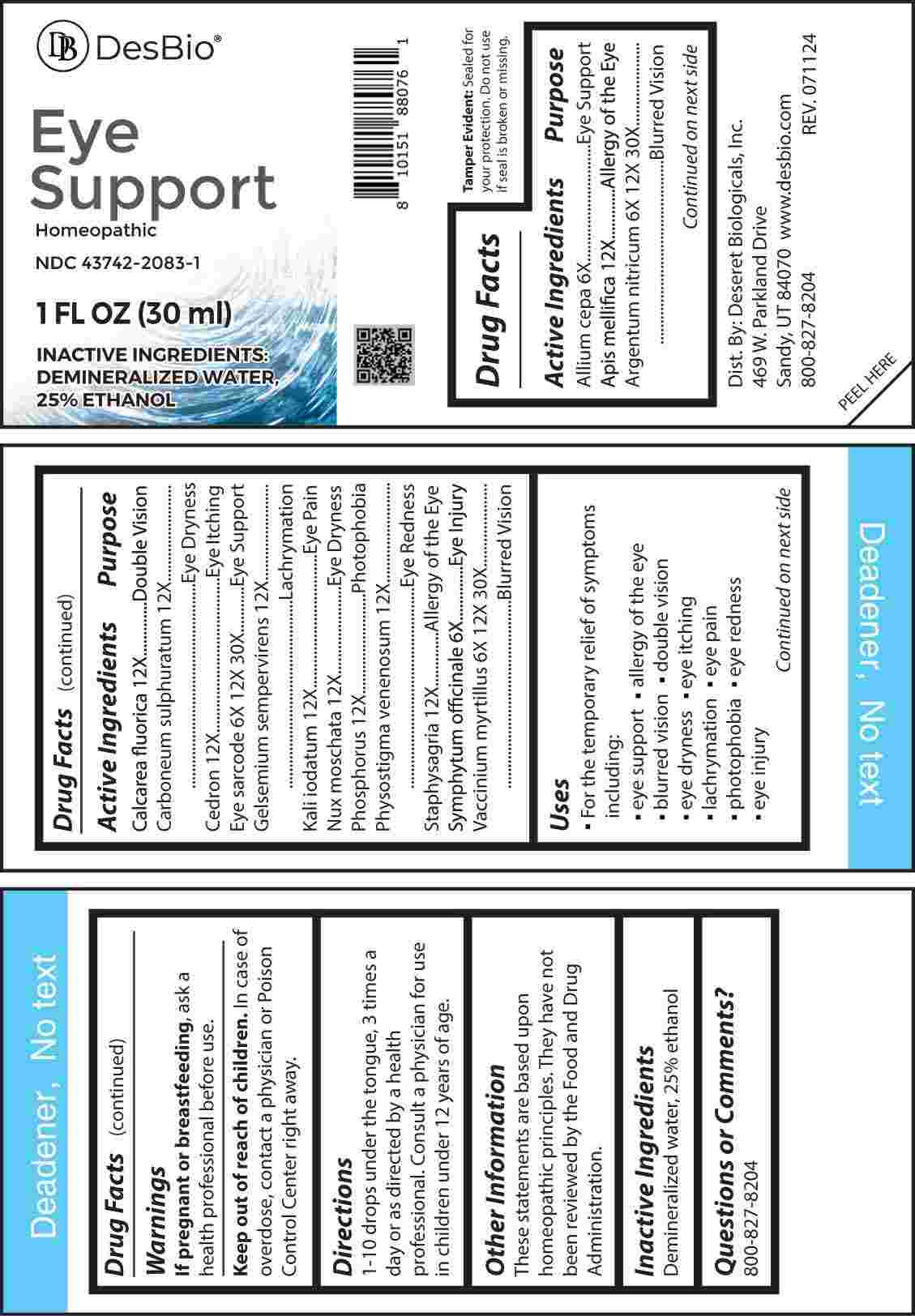 DRUG LABEL: Eye Support
NDC: 43742-2083 | Form: LIQUID
Manufacturer: Deseret Biologicals, Inc.
Category: homeopathic | Type: HUMAN OTC DRUG LABEL
Date: 20241023

ACTIVE INGREDIENTS: ONION 6 [hp_X]/1 mL; COMFREY ROOT 6 [hp_X]/1 mL; SILVER NITRATE 6 [hp_X]/1 mL; SUS SCROFA EYE 6 [hp_X]/1 mL; BILBERRY 6 [hp_X]/1 mL; APIS MELLIFERA 12 [hp_X]/1 mL; CALCIUM FLUORIDE 12 [hp_X]/1 mL; CARBON DISULFIDE 12 [hp_X]/1 mL; HOMALOLEPIS CEDRON SEED 12 [hp_X]/1 mL; GELSEMIUM SEMPERVIRENS ROOT 12 [hp_X]/1 mL; POTASSIUM IODIDE 12 [hp_X]/1 mL; NUTMEG 12 [hp_X]/1 mL; PHOSPHORUS 12 [hp_X]/1 mL; PHYSOSTIGMA VENENOSUM SEED 12 [hp_X]/1 mL; DELPHINIUM STAPHISAGRIA SEED 12 [hp_X]/1 mL
INACTIVE INGREDIENTS: WATER; ALCOHOL

DRUG FACTS:

ACTIVE INGREDIENTS:

Allium Cepa 6X, Apis Mellifica 12X, Argentum Nitricum 6X, 12X, 30X, Calcarea Fluorica 12X, Carboneum Sulphuratum 12X, Cedron 12X, Eye Sarcode 6X, 12X, 30X, Gelsemium Sempervirens 12X, Kali Iodatum 12X, Nux Moschata 12X, Phosphorus 12X, Physostigma Venenosum 12X, Staphysagria 12X, Symphytum Officinale 6X, Vaccinium Myrtillus 6X, 12X, 30X.

PURPOSE:

Allium Cepa – Eye Support, Apis Mellifica – Allergy of the Eye, Argentum Nitricum – Blurred Vision, Calcarea Fluorica – Double
Vision, Carboneum Sulphuratum – Eye Dryness, Cedron – Eye Itching, Eye Sarcode – Eye Support, Gelsemium Sempervirens - Lachrymation, Kali Iodatum – Eye Pain, Nux Moschata – Eye Dryness, Phosphorus - Photophobia, Physostigma Venenosum – Eye Redness, Staphysagria – Allergy of the Eye, Symphytum Officinale – Eye Injury, Vaccinium Myrtillus – Blurred Vision.

INDICATIONS:

• For the temporary relief of symptoms including:

• eye support • allergy of the eye • blurred vision

• double vision • eye dryness • eye itching

• lachrymation • eye pain • Photophobia

• eye redness • eye injury

These statements are based upon homeopathic principles. They have not been reviewed by the Food and Drug Administration.

WARNINGS:

If pregnant or breast-feeding, ask a health professional before use.

Keep out of reach of children. In case of overdose, contact a physician or Poison Control Center right away.

Tamper Evident: Sealed for your protection. Do not use if seal is broken or missing.

KEEP OUT OF REACH OF CHILDREN:

In case of overdose, contact a physician or Poison Control Center right away.

DIRECTIONS:

1-10 drops under the tongue, 3 times a day or as directed by a health professional. Consult a physician for use in children under 12 years of age.

INACTIVE INGREDIENTS:

Demineralized water, 25% ethanol

QUESTIONS:

Dist. By: Deseret Biologicals, Inc.
469 W. Parkland Drive
Sandy, UT 84070

www.desbio.com

800-827-8204

PACKAGE LABEL DISPLAY:

DesBio

Eye Support

Homeopathic

NDC 43742-2083-1

1 FL OZ (30 ml)